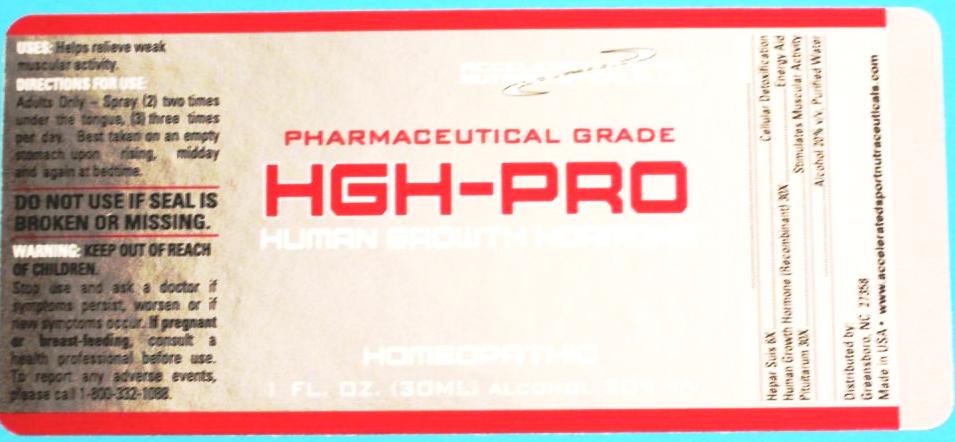 DRUG LABEL: HGH-Pro
NDC: 50845-0084 | Form: SPRAY
Manufacturer: Liddell Laboratories
Category: homeopathic | Type: HUMAN OTC DRUG LABEL
Date: 20101001

ACTIVE INGREDIENTS: SOMATROPIN 30 [hp_X]/1 mL; PORK LIVER 6 [hp_X]/1 mL; SUS SCROFA PITUITARY GLAND 30 [hp_X]/1 mL
INACTIVE INGREDIENTS: WATER; ALCOHOL

HGH-Pro

ACTIVE INGREDIENT

ACTIVE INGREDIENTS: HGH 30X, Hepar suis 6X, Pituitarium 30X.

PURPOSE

USES: Helps relieve weak muscular activity.

WARNINGS: KEEP OUT OF REACH OF CHILDREN.

Stop use and ask a doctor is symptoms persist, worsen or if new symptoms occur.

If pregnant or breast-feeding, consult a health professional before use. To report any adverse events, please call 1-800-332-1088.

Do not use if seal is broken or missing.

DOSAGE AND ADMINISTRATION

DIRECTIONS FOR USE: Adults Only - Spray (2) two times under the tongue, (3) three times per day. Best taken on an empty stomach upon rising, midday and again at bedtime.

INACTIVE INGREDIENTS: Alcohol 20%v/v, Purified water.

KEEP OUT OF REACH OF CHILDREN.

INDICATIONS AND USAGE

USES: Helps relieve weak muscular activity.

QUESTIONS

Distributed by:

Greensboto, NC 27358

www.acceleratedsportnutraceuticals.com

PACKAGE LABEL

ACCELERATED SPORT NUTRACEUTICALS, LLC

PHARMACEUTICAL GRADE

HGH-PRO

HUMAN GROWTH HORMONE

HOMEOPATHIC

1 FL. OZ. (30 ml)